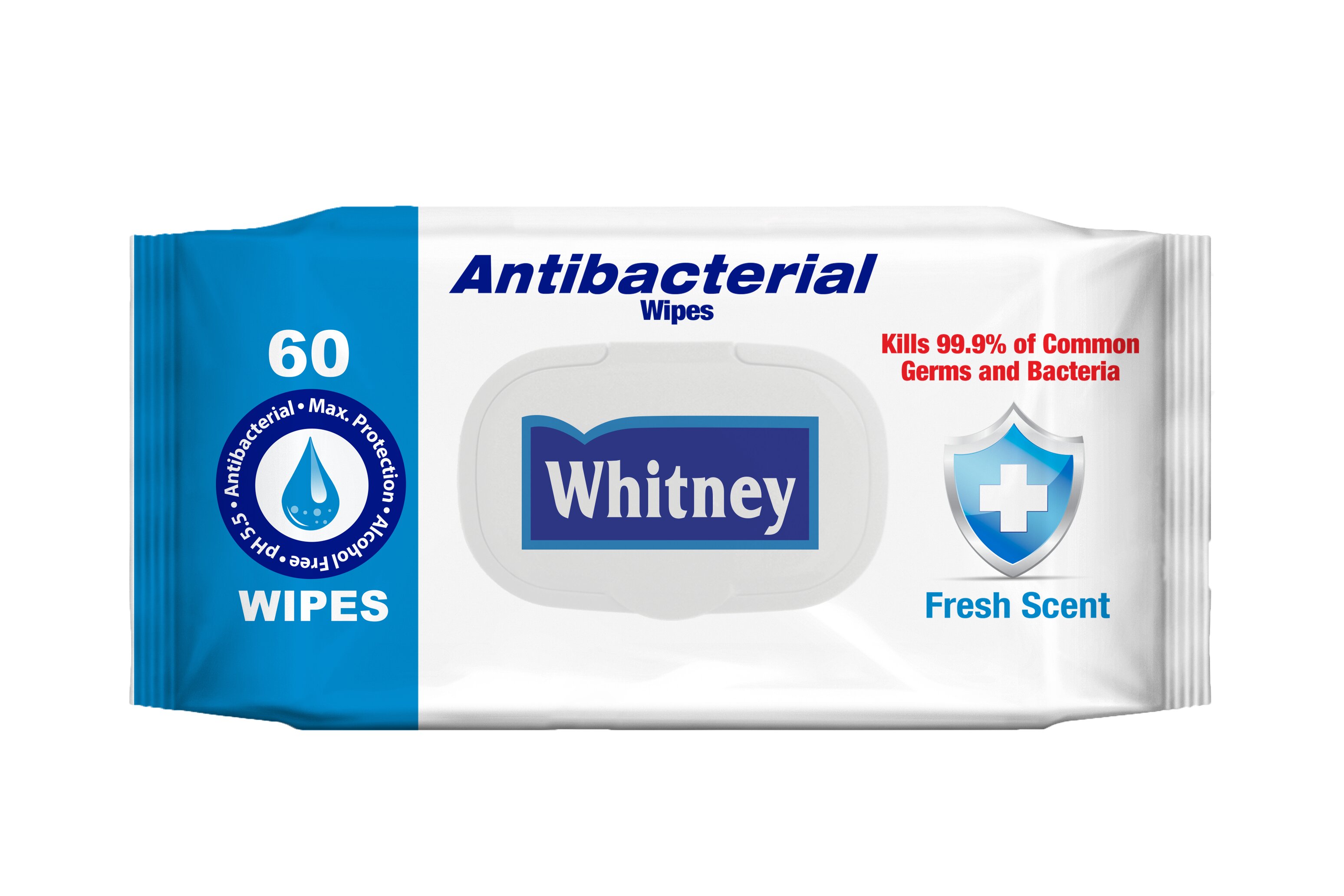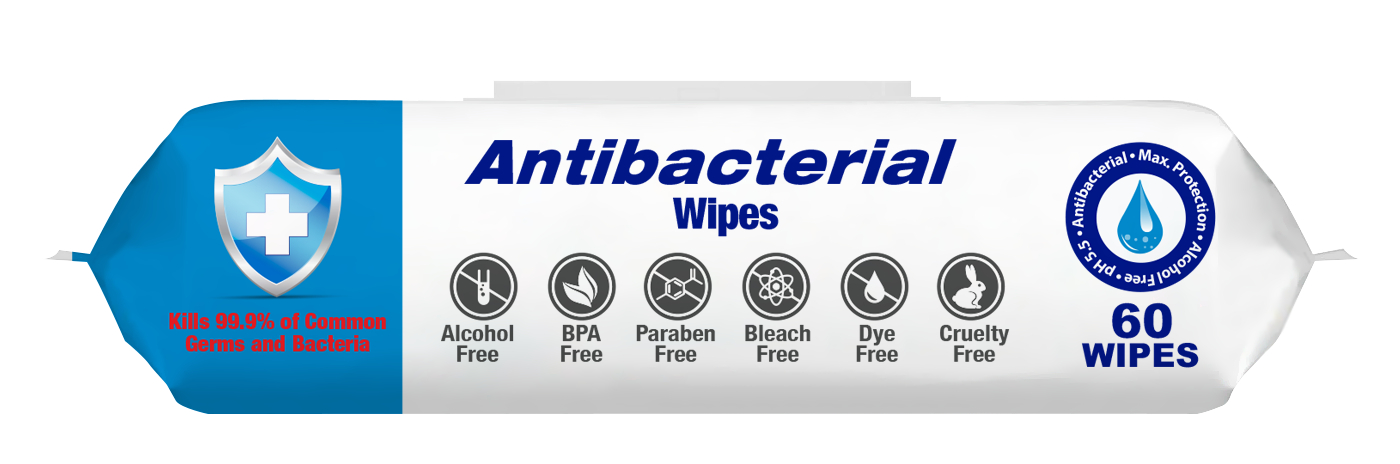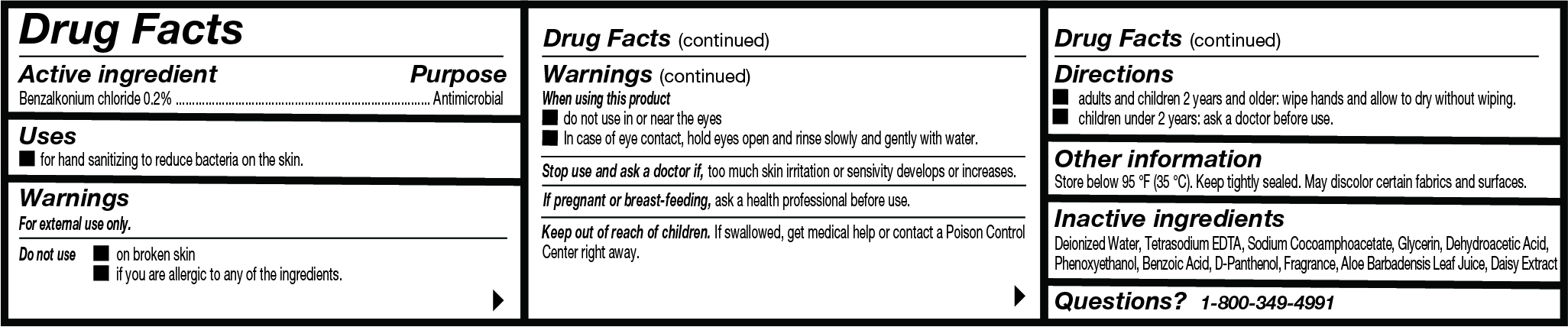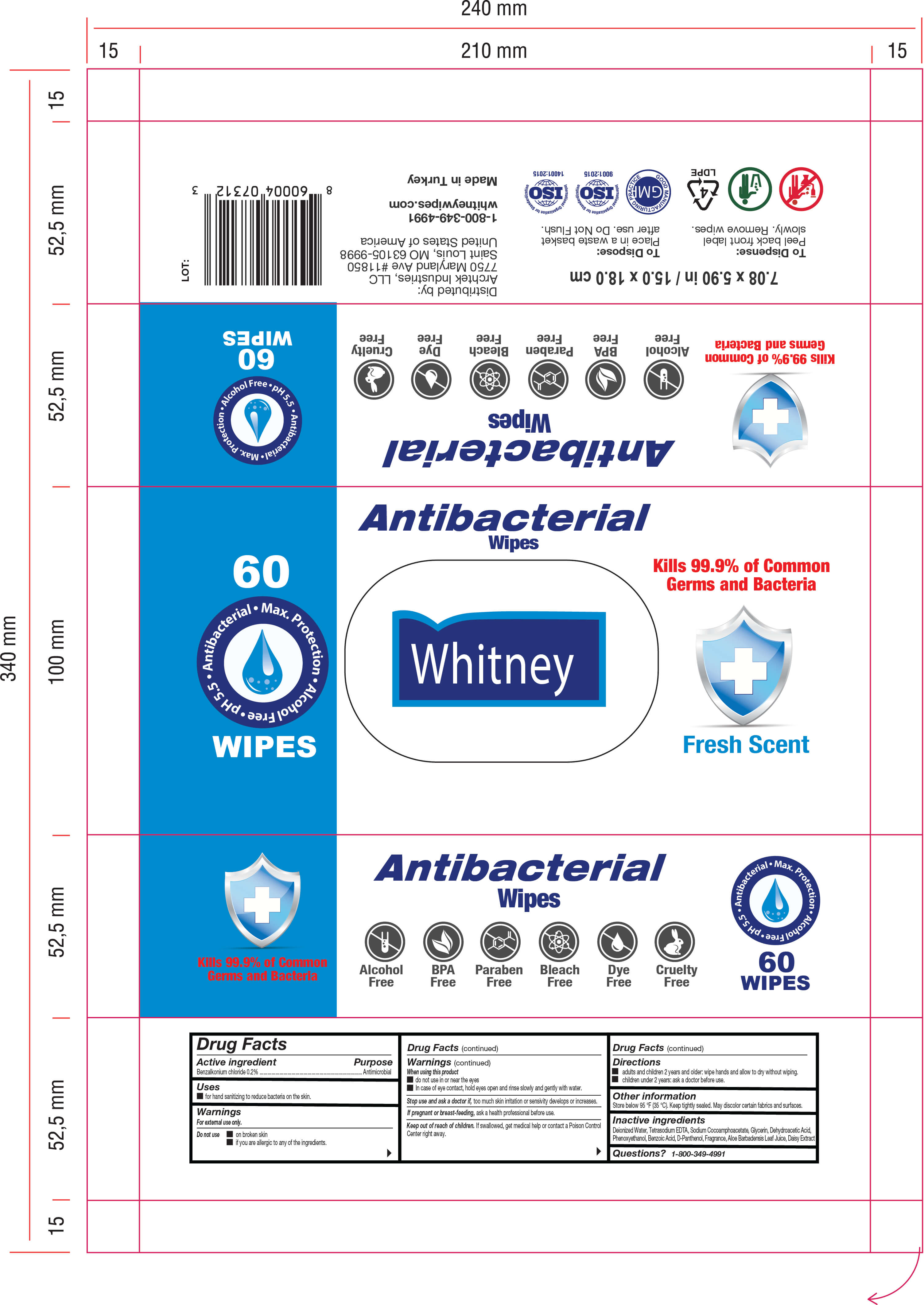 DRUG LABEL: Antibacterial Wipes
NDC: 79084-001 | Form: SWAB
Manufacturer: GULSELI TEMIZLIK URUNLERI SANAYI VE TICARET ANONIM SIRKETI
Category: otc | Type: HUMAN OTC DRUG LABEL
Date: 20200618

ACTIVE INGREDIENTS: BENZALKONIUM CHLORIDE 0.2 g/100 g
INACTIVE INGREDIENTS: EDETATE SODIUM; ALOE VERA LEAF; BELLIS PERENNIS FLOWER; PHENOXYETHANOL; DEXPANTHENOL; BENZOIC ACID; GLYCERIN; DEHYDROACETIC ACID; SODIUM COCOAMPHOACETATE; WATER

Antibacterial Wipes

INACTIVE INGREDIENT

Deionized Water, Tetrasodium EDTA, Sodium Cocoamphoacetate, Glycerin, Dehydroacetic Acid,
Phenoxyethanol, Benzoic Acid, D-Panthenol, Fragrance, Aloe Barbadensis Leaf Juice, Daisy Extrac

PURPOSE

Antimicrobial

Keep out of reach of children. If swallowed, get medical help or contact a Poison Control Center right away.

ACTIVE INGREDIENT

Benzalkonium chloride 0.2% w/w

- do not use in or near the eyes
- In case of eye contact, hold eyes open and rinse slowly and gently with water.

PREGNANCY OR BREAST FEEDING

If pregnant or breast-feeding, ask a health professional before use.

DO NOT USE

- on broken skin
- if you are allergic to any of the ingredients.

Stop use and ask a doctor if, too much skin irritation or sensivity develops or increases.

DOSAGE AND ADMINISTRATION

adults and children 2 years and older: wipe hands and allow to dry without wiping.
children under 2 years: ask a doctor before use.

INDICATIONS AND USAGE

for hand sanitizing to reduce bacteria on the skin.

WARNINGS

For external use only.